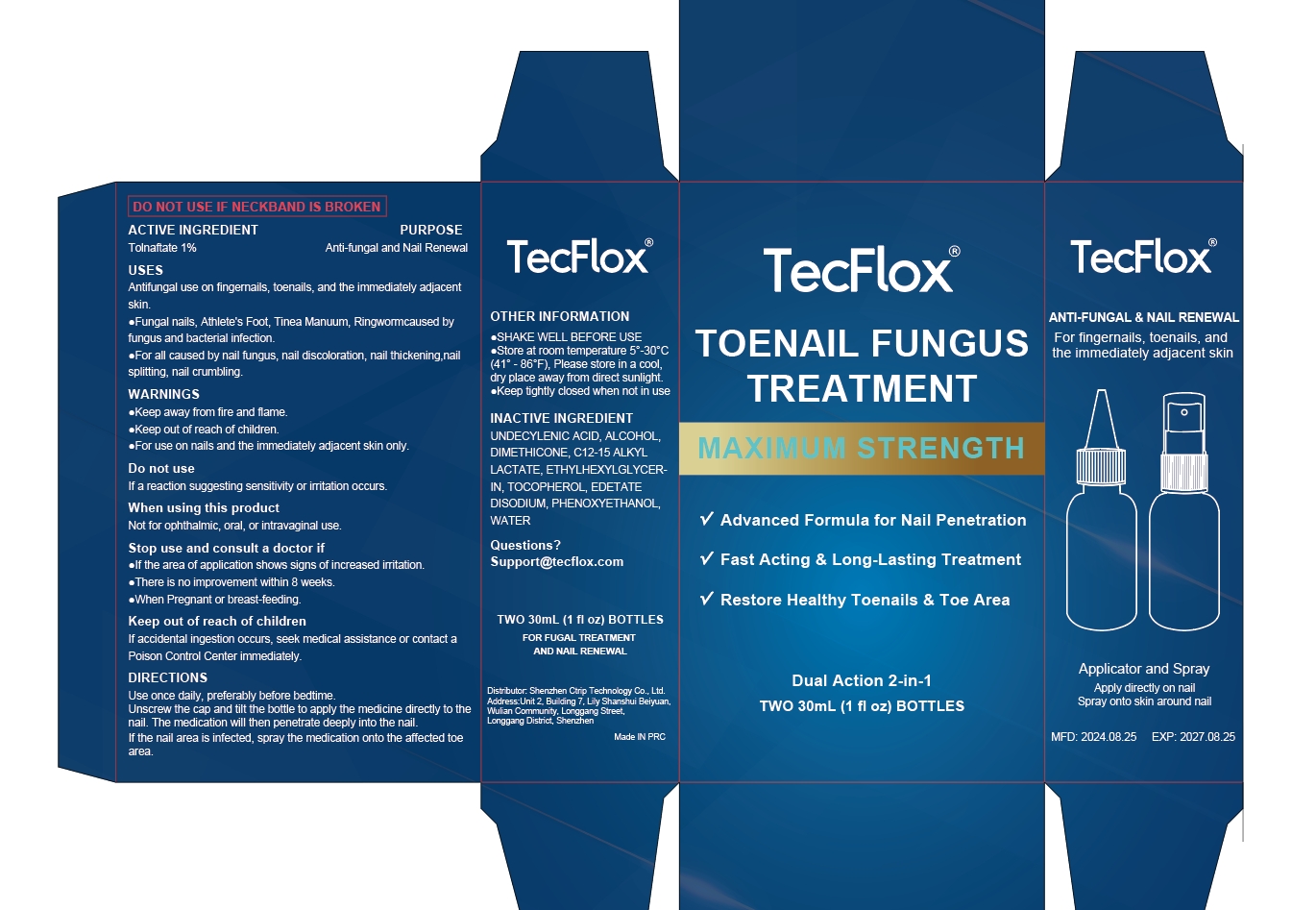 DRUG LABEL: TOENAIL FUNGUS TREATMENT MAXIMUM STRENGTH Liquid
NDC: 84614-002 | Form: LIQUID
Manufacturer: Shenzhen Ctrip Technology Co., Ltd.
Category: otc | Type: HUMAN OTC DRUG LABEL
Date: 20260119

ACTIVE INGREDIENTS: TOLNAFTATE 1 g/100 mL
INACTIVE INGREDIENTS: UNDECYLENIC ACID; ALCOHOL; WATER; TOCOPHEROL; PHENOXYETHANOL; EDETATE DISODIUM; DIMETHICONE; C12-15 ALKYL LACTATE; ETHYLHEXYLGLYCERIN

84614-002 TOENAIL FUNGUS TREATMENT MAXIMUM STRENGTH Liquid

TOENAIL FUNGUS TREATMENT MAXIMUM STRENGTH Liquid

ACTIVE INGREDIENT

Tolnaftate 1%

PURPOSE

Anti-fungal and Nail Renewal

INDICATIONS AND USAGE

Antifungal use on fingemails, toenails, and the immediately adjacent skin.
Fungal nails, Athlete's Foot, Tinea Manuum, Ringwomcaused byfungus and bacterial infection.
For all caused by nail fungus, nail discoloration, nail thickening,nailsplitting, nail crumbling

WARNINGS

Keep away from fire and flame.
Keep out of reach of children.
For use on nails and the immediately adjacent skin only.

DO NOT USE

If a reaction suggesting sensitivity or iritation occurs.

WHEN USING

Not for ophthalmic, oral, or intravaginal use

STOP USE

lf the area of application shows signs of increased iritation.
There is no improvement within 8 weeks.
When Pregnant or breast-feeding

KEEP OUT OF REACH OF CHILDREN

If accidental ingestion occurs, seek medical assistance or contact a Poison Control Center immediately.

DOSAGE AND ADMINISTRATION

Use once daily, preferably before bedtimeUnscrew the cap and tilt the bottle to apply the medicine directly to thenail. The medication will then penetrate deeply into the nail.If the nail area is infected, spray the medication onto the affected toearea.

STORAGE AND HANDLING

SHAKE WELL BEFORE USE
Store at room temperature 5--30°C(41°-86°F), Please store in a cool,dry place away from direct sunlight.
Keep tightly closed when not in use

INACTIVE INGREDIENT

UNDECYLENIC ACID
ALCOHOL
DIMETHICONE
C12-15 ALKYL LACTATE
ETHYLHEXYLGLYCERIN
TOCOPHEROL
EDETATE DISODIUM
PHENOXYETHANOL
WATER